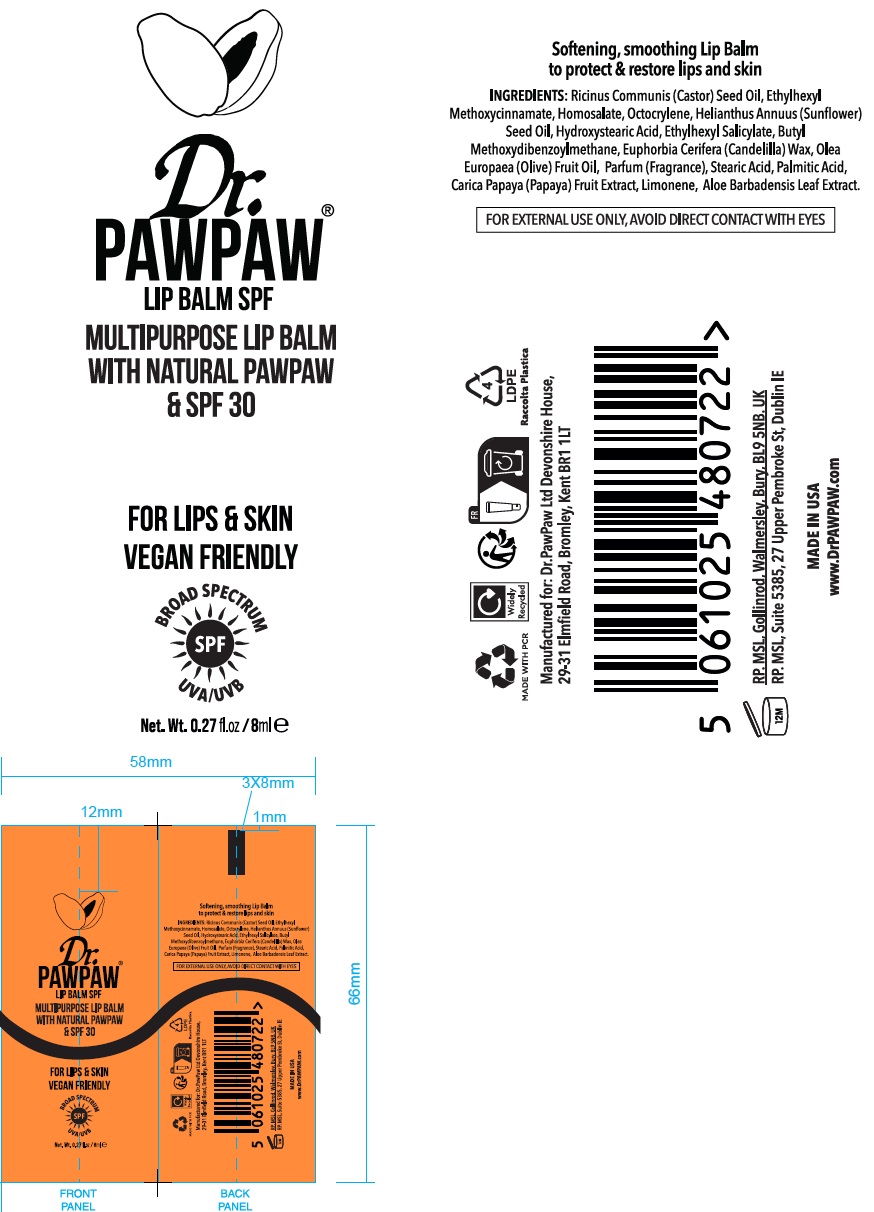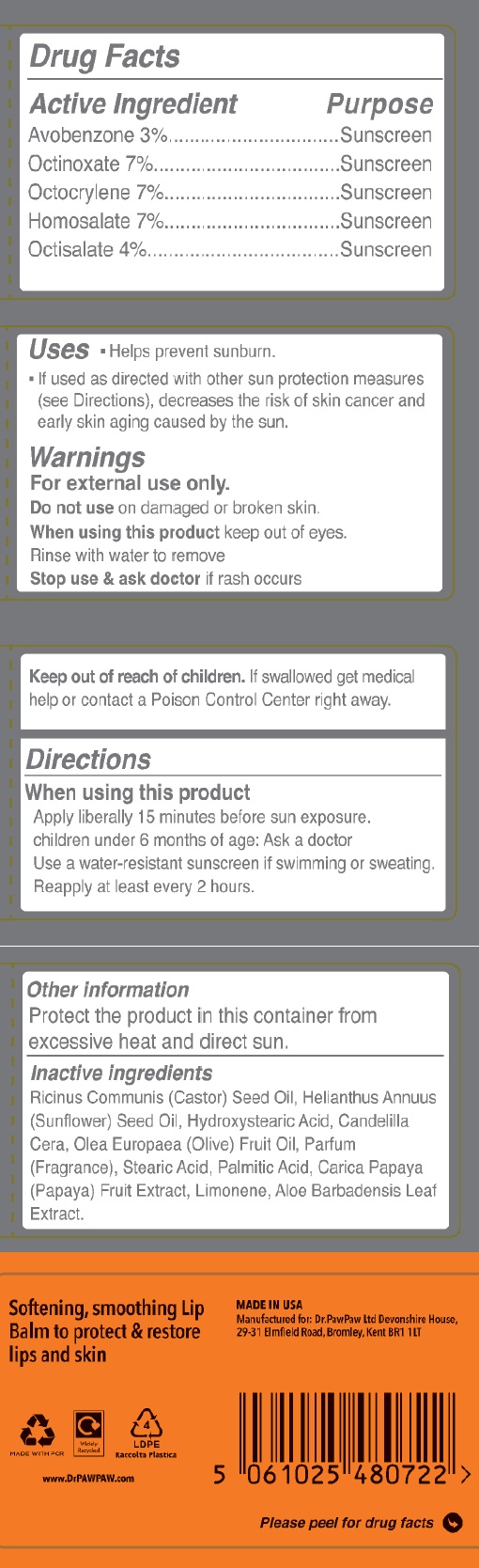 DRUG LABEL: Dr Pawpaw MultiPurpose Lip Balm with natural PawPaw and SPF 30
NDC: 84572-000 | Form: CREAM
Manufacturer: Dr Pawpaw Limited
Category: otc | Type: HUMAN OTC DRUG LABEL
Date: 20240725

ACTIVE INGREDIENTS: AVOBENZONE 30 mg/1 mL; OCTINOXATE 70 mg/1 mL; OCTOCRYLENE 70 mg/1 mL; HOMOSALATE 70 mg/1 mL; OCTISALATE 40 mg/1 mL
INACTIVE INGREDIENTS: CASTOR OIL; SUNFLOWER OIL; 12-HYDROXYSTEARIC ACID; CANDELILLA WAX; OLIVE OIL; STEARIC ACID; PALMITIC ACID; PAPAYA; LIMONENE, (+)-; ALOE VERA LEAF

Dr. Pawpaw MultiPurpose Lip Balm with natural PawPaw & SPF 30

Active Ingredient

Avobenzone 3%

Octinoxate 7%

Octocrylene 7%

Homosalate 7%

Octisalate 4%

Purpose

Sunscreen

Uses

- Helps prevent sunburn.
- If used as directed with other sun protection measures (see Directions), decreases the risk of skin cancer and early skin aging caused by the sun.

Warnings

For external use only.

Do not use

on damaged or broken skin.

When using this product

keep out of eyes. Rinse with water to remove

Stop use & ask doctor

if rash occurs

Keep out of reach of children.

If swallowed get medical help or contact a Poison Control Center right away.

Directions

When using this product

Apply liberally 15 minutes before sun exposure. children under 6 months of age: Ask a doctor Use a water-resistant sunscreen if swimming or sweating. Reapply at least every 2 hours.

Other information

Protect the product in this container from excessive heat and direct sun.

Inactive ingredients

Ricinus Communis (Castor) Seed Oil, Helianthus Annuus (Sunflower) Seed Oil, Hydroxystearic Acid, Candelilla Cera, Olea Europaea (Olive) Fruit Oil, Parfum (Fragrance), Stearic Acid, Palmitic Acid, Carica Papaya (Papaya) Fruit Extract, Limonene, Aloe Barbadensis Leaf Extract.